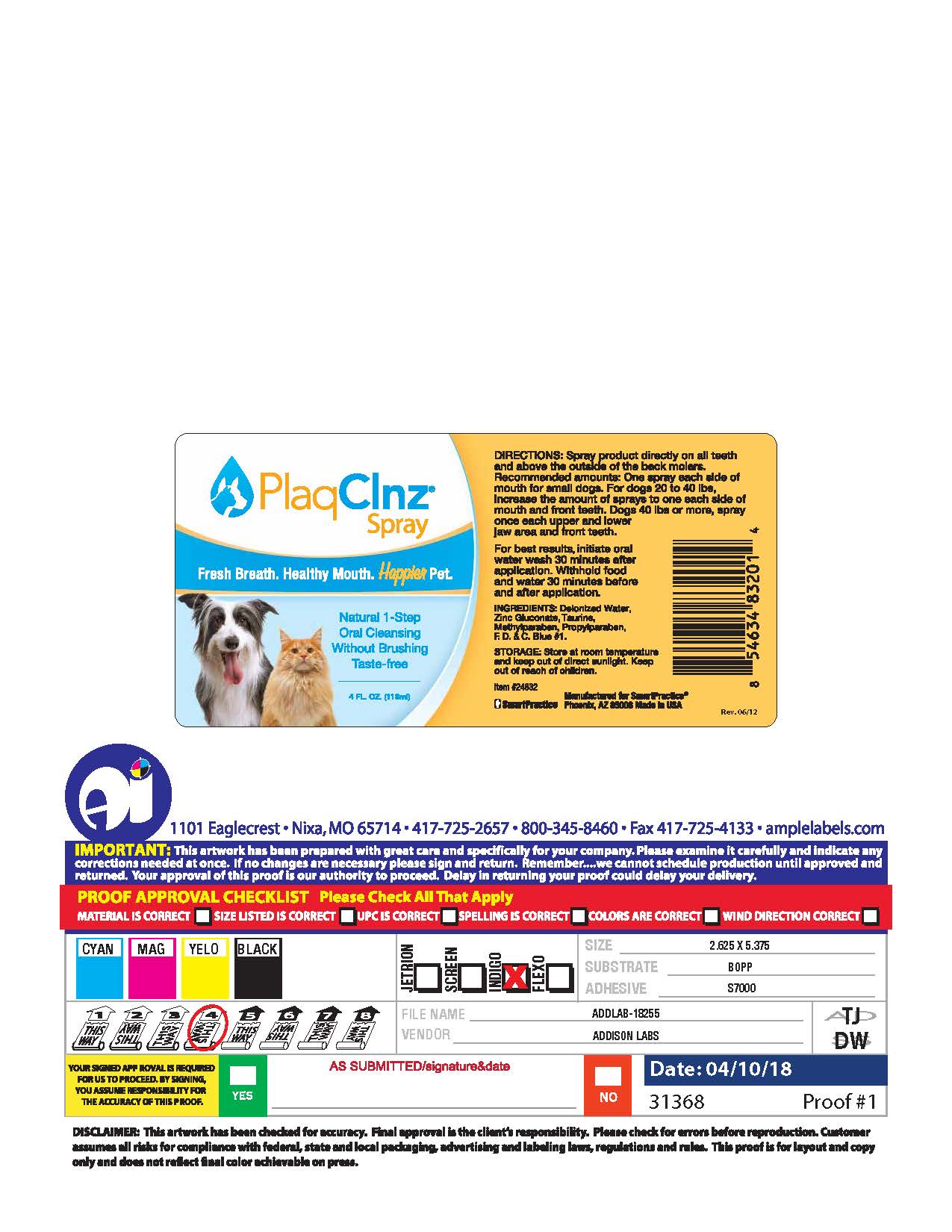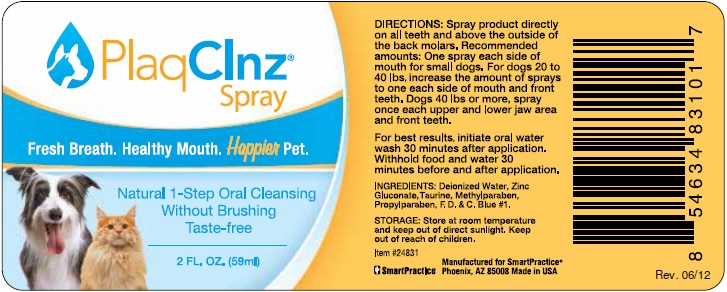 DRUG LABEL: PlaqClnz
NDC: 69521-001 | Form: SPRAY
Manufacturer: SmartHealth, Inc. (DBA SmartPractice)
Category: animal | Type: OTC ANIMAL DRUG LABEL
Date: 20251219

ACTIVE INGREDIENTS: Zinc Gluconate 0.0165 g/1 mL
INACTIVE INGREDIENTS: WATER; TAURINE; METHYLPARABEN; PROPYLPARABEN; FD&C BLUE NO. 1

PlaqClnz® Spray

DOSAGE AND ADMINISTRATION

DIRECTIONS: Spray product directly on all teeth and above the outside of the back molars. Recommended amounts: One spray each side of mouth for small dogs. For dogs 20 to 40lbs, increase the amount of sprays to one each side of mouth and front teeth. Dogs 40 lbs or more, spray once each upper and lower jaw area and front teeth.

For best results initiate oral water wash 30 minutes after application. Withhold food and water 30 minutes before and after application.

DESCRIPTION

INGREDIENTS: Deionized Water, Zinc Gluconate, Taurine, Methylparaben, Propylparaben, F. D. & C. Blue #1.

STORAGE AND HANDLING

STORAGE: Store at room temperature and keep out of direct sunlight. Keep out of reach of children.

SmartPractice

Manufactured for SmartPractice®
Phoenix, AZ 85008 Made in USA

PACKAGE LABEL

PlaqClnz®
Spray

Fresh Breath. Healthy Mouth. Happier Pet.

Natural 1-Step Oral Cleansing
Without Brushing
Taste-free

2 FL. OZ. (59ml)

DIRECTIONS: Spray product directly on all teeth and above the outside of the back molars. Recommended amounts: One spray each side of mouth for small dogs. For dogs 20 to 40lbs, increase the amount of sprays to one each side of mouth and front teeth. Dogs 40 lbs or more, spray once each upper and lower jaw area and front teeth.

For best results initiate oral water wash 30 minutes after application. Withhold food and water 30 minutes before and after application.

INGREDIENTS: Deionized Water, Zinc Gluconate, Taurine, Methylparaben, Propylparaben, F. D. & C. Blue #1.

STORAGE: Store at room temperature and keep out of direct sunlight. Keep out of reach of children.

Item #24831

SmartPractice

Manufactured for SmartPractice®
Phoenix, AZ 85008 Made in USA

PACKAGE LABEL

PlaqClnz®
Spray

Fresh Breath. Healthy Mouth. Happier Pet.

Natural 1-Step Oral Cleansing
Without Brushing
Taste-free

4 FL. OZ. (118ml)

DIRECTIONS: Spray product directly on all teeth and above the outside of the back molars. Recommended amounts: One spray each side of mouth for small dogs. For dogs 20 to 40lbs, increase the amount of sprays to one each side of mouth and front teeth. Dogs 40 lbs or more, spray once each upper and lower jaw area and front teeth.

For best results initiate oral water wash 30 minutes after application. Withhold food and water 30 minutes before and after application.

INGREDIENTS: Deionized Water, Zinc Gluconate, Taurine, Methylparaben, Propylparaben, F. D. & C. Blue #1.

STORAGE: Store at room temperature and keep out of direct sunlight. Keep out of reach of children.

Item #24832

SmartPractice

Manufactured for SmartPractice®
Phoenix, AZ 85008 Made in USA